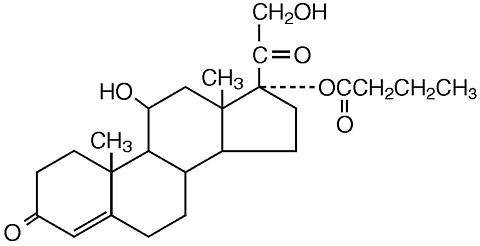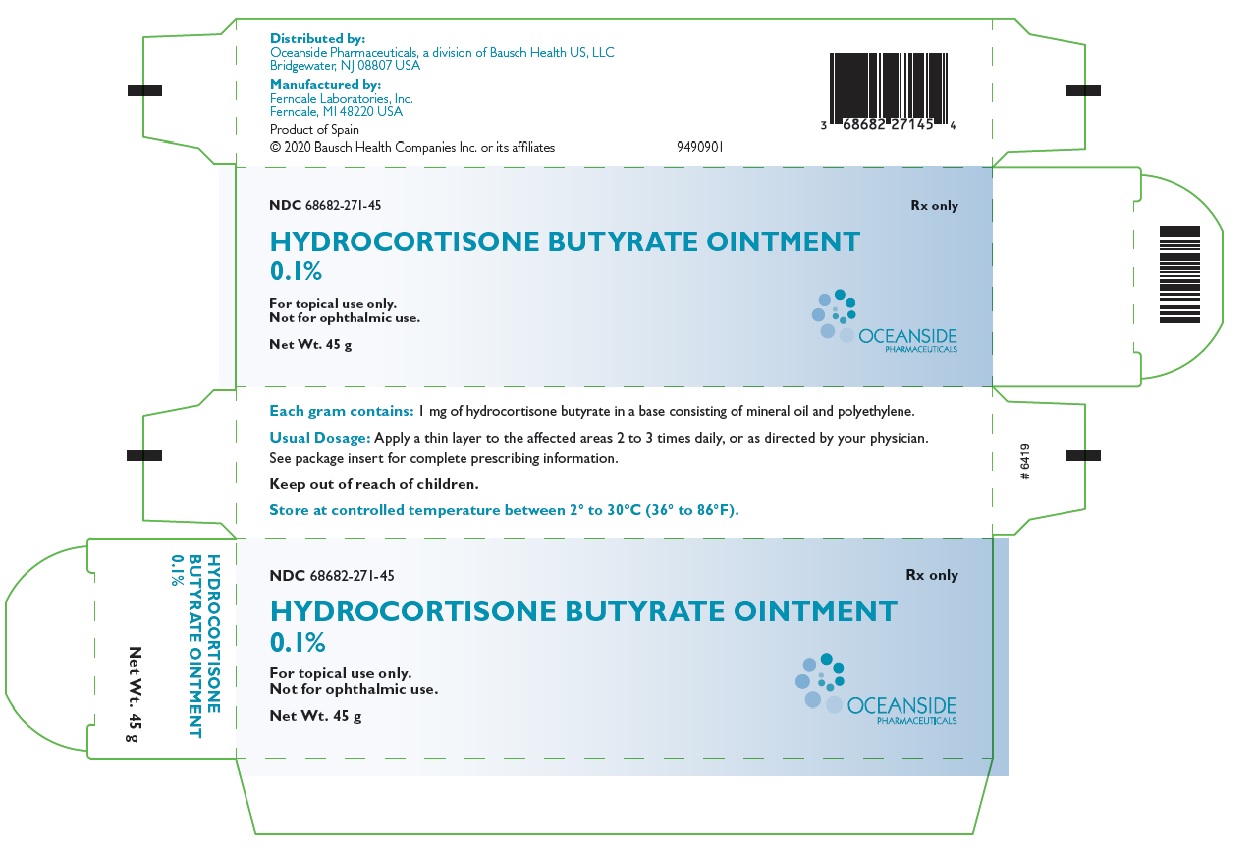 DRUG LABEL: Hydrocortisone Butyrate
NDC: 68682-271 | Form: OINTMENT
Manufacturer: Oceanside Pharmaceuticals
Category: prescription | Type: HUMAN PRESCRIPTION DRUG LABEL
Date: 20201231

ACTIVE INGREDIENTS: HYDROCORTISONE BUTYRATE 1 mg/1 g
INACTIVE INGREDIENTS: MINERAL OIL; POLYETHYLENE GLYCOL, UNSPECIFIED

Hydrocortisone Butyrate
Ointment, 0.1%
For topical use only.
Not for ophthalmic use.

DESCRIPTION

Hydrocortisone Butyrate Ointment, 0.1% contains the topical corticosteroid, hydrocortisone butyrate, a non-fluorinated hydrocortisone ester. It has the chemical name: 11β,17,21-Trihydroxypregn-4-ene-3,20-dione 17-butyrate; the molecular formula: C25H36O6; the molecular weight: 432.54; and the CAS registry number: 13609-67-1.

Its structural formula is:

Each gram of Hydrocortisone Butyrate Ointment contains 1 mg of hydrocortisone butyrate in a base consisting of mineral oil and polyethylene.

CLINICAL PHARMACOLOGY

Topical corticosteroids share anti-inflammatory, anti-pruritic, and vasoconstrictive actions. The mechanism of anti-inflammatory activity of topical corticosteroids is unclear. Various laboratory methods, including vasoconstrictor assays, are used to compare and predict potencies and/or clinical efficacies of topical corticosteroids. There is some evidence to suggest that a recognizable correlation exists between vasoconstrictor potency and therapeutic efficacy in man.

Pharmacokinetics

The extent of percutaneous absorption of topical corticosteroids is determined by many factors including the vehicle, the integrity of the epidermal barrier, and the use of occlusive dressings.

Topical corticosteroids can be absorbed from normal intact skin. Inflammation and/or other disease processes in the skin increase percutaneous absorption. Occlusive dressings substantially increase the percutaneous absorption of topical corticosteroids.

Once absorbed through the skin, topical corticosteroids are handled through pharmacokinetic pathways similar to systemically administered corticosteroids. Corticosteroids are bound to plasma proteins in varying degrees. Corticosteroids are metabolized primarily in the liver and are then excreted by the kidneys. Some of the topical corticosteroids and their metabolites are also excreted into the bile.

INDICATIONS AND USAGE

Hydrocortisone Butyrate Ointment, 0.1% is indicated for the relief of the inflammatory and pruritic manifestations of corticosteroid-responsive dermatoses.

CONTRAINDICATIONS

None.

PRECAUTIONS

General

Systemic absorption of topical corticosteroids has produced reversible hypothalamic-pituitary-adrenal (HPA) axis suppression, manifestations of Cushing’s syndrome, hyperglycemia, and glucosuria in some patients. Conditions which augment systemic absorption include the application of the more potent corticosteroids, use over large surface areas, prolonged use, and the addition of occlusive dressings.

Therefore, patients receiving a large dose of a potent topical corticosteroid applied to a large surface area or under an occlusive dressing should be evaluated periodically for evidence of HPA-axis suppression by using adrenocorticotropic hormone (ACTH) stimulation tests.

If HPA-axis suppression is noted, an attempt should be made to withdraw the drug, to reduce the frequency of application, or to substitute a less potent corticosteroid.

Recovery of HPA-axis function is generally prompt and complete upon discontinuation of the drug.

Infrequently, signs and symptoms of corticosteroid withdrawal may occur, requiring supplemental systemic corticosteroids.

Children may absorb proportionally larger amounts of topical corticosteroids and thus be more susceptible to systemic toxicity. [See PRECAUTIONS, Pediatric Use.]

If irritation develops, topical corticosteroids should be discontinued and appropriate therapy instituted.

In the presence of dermatological infections, the use of an appropriate antifungal or antibacterial agent should be instituted. If a favorable response does not occur promptly, the corticosteroid should be discontinued until the infection has been adequately controlled.

Information for Patients

Patients using topical corticosteroids should receive the following information and instructions:

1. This medication is to be used as directed by the physician. It is for external use only. Avoid contact with the eyes.
2. Patients should be advised not to use this medication for any disorder other than that for which it was prescribed.
3. The treated skin area should not be bandaged or otherwise covered or wrapped as to be occlusive unless directed by the physician.
4. Patients should report any signs of local adverse reactions especially under occlusive dressing.
5. Parents of pediatric patients should be advised not to use tight-fitting diapers or plastic pants on a child being treated in the diaper area, as these garments may constitute occlusive dressings.

Carcinogenesis, Mutagenesis, Impairment of Fertility

Note: The animal multiples of human exposure calculations in this label were based on body surface area comparisons for an adult (i.e., mg/m^2/day dose comparisons) assuming 100% human percutaneous absorption of a maximum topical human dose (MTHD) for hydrocortisone butyrate ointment (25 g).

In a 2-year dermal rat carcinogenicity study with LOCOID® lotion, hydrocortisone butyrate was administered to Sprague-Dawley rats at topical doses of 0.05, 0.15, and 0.3 mg/kg/day in males and 0.1, 0.25, and 0.5 mg/kg/day in females (0.1% lotion). No drug-related tumors were noted in this study up to the highest doses evaluated in this study of 0.3 mg/kg/day in males (0.1X MTHD) and 0.5 mg/kg/day in females (0.2X MTHD).

Hydrocortisone butyrate revealed no evidence of mutagenic or clastogenic potential based on the results of two in vitrogenotoxicity tests (Ames test and L5178Y/TK+/- mouse lymphoma assay) and one in vivogenotoxicity test (mouse micronucleus assay).

No evidence of impairment of fertility or effect on mating performance was observed in a fertility and general reproductive performance study conducted in male and female rats at subcutaneous doses up to and including 1.8 mg/kg/day (0.7X MTHD). Mild effects on maternal animals, such as reduced food consumption and a subsequent reduction in body weight gain, were seen at doses ≥0.6 mg/kg/day (0.2X MTHD).

Teratogenic Effects

Corticosteroids are generally teratogenic in laboratory animals when administered systemically at relatively low dosage levels. The more potent corticosteroids have been shown to be teratogenic after dermal application in laboratory animals. There are no adequate and well-controlled studies in pregnant women on teratogenic effects from topically applied corticosteroids. Therefore, topical corticosteroids should be used during pregnancy only if the potential benefit justifies the potential risk to the fetus.

Drugs of this class should not be used extensively on pregnant patients, in large amounts, or for prolonged periods of time.

Systemic embryofetal development studies were conducted in rats and rabbits. Subcutaneous doses of 0.6, 1.8, and 5.4 mg/kg/day hydrocortisone butyrate were administered to pregnant female rats during gestation days 6 – 17. In the presence of maternal toxicity, fetal effects noted at 5.4 mg/kg/day (2X MTHD) included an increased incidence of ossification variations and unossified sternebra. No treatment-related effects on embryofetal toxicity or teratogenicity were noted at doses of 5.4 and 1.8 mg/kg/day, respectively (2X MTHD and 0.7X MTHD, respectively).

Subcutaneous doses of 0.1, 0.2, and 0.3 mg/kg/day hydrocortisone butyrate were administered to pregnant female rabbits during gestation days 7 – 20. An increased incidence of abortion was noted at 0.3 mg/kg/day (0.2X MTHD). In the absence of maternal toxicity, a dose-dependent decrease in fetal body weight was noted at doses ≥0.1 mg/kg/day (0.1X MTHD). Additional indicators of embryofetal toxicity (i.e., reduction in litter size, decreased number of viable fetuses, increased post-implantation loss) were noted at doses ≥0.2 mg/kg/day (0.2X MTHD). Additional fetal effects noted in this study included delayed ossification noted at doses ≥0.1 mg/kg/day and an increased incidence of fetal malformations (primarily skeletal malformations) noted at doses ≥0.2 mg/kg/day. A dose at which no treatment-related effects on embryofetal toxicity or teratogenicity were observed was not established in this study.

Additional systemic embryofetal development studies were conducted in rats and mice. Subcutaneous doses of 0.1 and 9 mg/kg/day hydrocortisone butyrate were administered to pregnant female rats during gestation days 9 – 15. In the presence of maternal toxicity, an increase in fetal deaths, fetal resorptions and an increase in the number of ossifications in caudal vertebrae were noted at a dose of 9 mg/kg/day (3X MTHD). No treatment-related effects on embryofetal toxicity or teratogenicity were noted at 0.1 mg/kg/day (0.1X MTHD).

Subcutaneous doses of 0.2 and 1 mg/kg/day hydrocortisone butyrate were administered to pregnant female mice during gestation days 7 – 13. In the absence of maternal toxicity, an increased number of cervical ribs and one fetus with clubbed legs were noted at a dose of 1 mg/kg/day (0.2X MTHD). No treatment-related effects on embryofetal toxicity or teratogenicity were noted at doses of 1 and 0.2 mg/kg/day, respectively (0.2X MTHD and 0.1X MTHD, respectively).

Topical embryofetal development studies were conducted in rats and rabbits with a hydrocortisone butyrate ointment formulation. Topical doses of 1% and 10% hydrocortisone butyrate ointment were administered to pregnant female rats during gestation days 6 – 15 or pregnant female rabbits during gestation days 6 – 18. A dose-dependent increase in fetal resorptions was noted in rabbits (0.2 – 2X MTHD) and fetal resorptions were noted in rats at the 10% hydrocortisone butyrate ointment dose (80X MTHD). No treatment-related effects on embryofetal toxicity were noted at the 1% hydrocortisone butyrate ointment dose in rats (8X MTHD). A dose at which no treatment-related effects on embryofetal toxicity were observed in rabbits after topical administration of hydrocortisone butyrate ointment was not established in this study. No treatment-related effects on teratogenicity were noted at a dose of 10% hydrocortisone butyrate ointment in rats or rabbits (80X MTHD and 2X MTHD, respectively).

A peri- and postnatal development study was conducted in rats. Subcutaneous doses of 0.6, 1.8, and 5.4 mg/kg/day hydrocortisone butyrate were administered to pregnant female rats from gestation day 6 to lactation day 20. In the presence of maternal toxicity, a dose-dependent decrease in fetal weight was noted at doses ≥1.8 mg/kg/day (0.7X MTHD). No treatment-related effects on fetal toxicity were noted at 0.6 mg/kg/day (0.2X MTHD).

A delay in sexual maturation was noted at 5.4 mg/kg/day (2X MTHD). No treatment-related effects on sexual maturation were noted at 1.8 mg/kg/day. No treatment-related effects on behavioral development or subsequent reproductive performance were noted at 5.4 mg/kg/day.

Nursing Mothers

It is not known whether topical administration of corticosteroids could result in sufficient systemic absorption to produce detectable quantities in breast milk. Systemically administered corticosteroids are secreted into breast milk, in quantities not likely to have a deleterious effect on the infant. Nevertheless, caution should be exercised when topical corticosteroids are administered to a nursing woman.

Pediatric Use

Pediatric patients may demonstrate greater susceptibility to topical corticosteroid-induced HPA-axis suppression and Cushing’s syndrome than mature patients because of a larger skin-surface-area-to-body-weight ratio.

Hypothalamic-pituitary-adrenal (HPA) axis suppression, Cushing’s syndrome, linear growth retardation, delayed weight gain, and intracranial hypertension have been reported in children receiving topical corticosteroids.

Manifestations of adrenal suppression in children include low plasma cortisol levels and absence of response to ACTH stimulation. Manifestations of intracranial hypertension include bulging fontanelles, headaches, and bilateral papilledema.

Administration of topical corticosteroids to children should be limited to the least amount compatible with an effective therapeutic regimen. Chronic corticosteroid therapy may interfere with the growth and development of children.

ADVERSE REACTIONS

The following local adverse reactions are reported infrequently with topical corticosteroids but may occur more frequently with the use of occlusive dressings. These reactions are listed in an approximate decreasing order of occurrence: burning, itching, irritation, dryness, folliculitis, hypertrichosis, acneiform eruptions, hypopigmentation, perioral dermatitis, allergic contact dermatitis, maceration of the skin, secondary infection, skin atrophy, striae, and miliaria.

To report SUSPECTED ADVERSE REACTIONS, contact Oceanside Pharmaceuticals at 1-800-321-4576 or FDA at 1-800-FDA-1088 or www.fda.gov/medwatch.

DOSAGE AND ADMINISTRATION

Hydrocortisone Butyrate Ointment, 0.1% should be applied to the affected areas as a thin layer 2 or 3 times daily depending on the severity of the condition. Occlusive dressings may be used for the management of psoriasis or recalcitrant conditions.

If an infection develops, the use of occlusive dressings should be discontinued and appropriate antimicrobial therapy instituted.

HOW SUPPLIED

Hydrocortisone Butyrate Ointment, 0.1% is supplied in tubes containing:

15 g (NDC 68682-271-15)
45 g (NDC 68682-271-45)

STORAGE

Store at controlled temperature between 2° to 30°C (36° to 86°F).

Distributed by:
Oceanside Pharmaceuticals, a division of
Bausch Health US, LLC
Bridgewater, NJ 08807 USA

Manufactured by:
Ferndale Laboratories, Inc.
Ferndale, MI 48220 USA

LOCOID is a trademark of Leo Pharma A/S used under license.
© 2020 Bausch Health Companies Inc. or its affiliates

9491001

Revised: 12/2020

PACKAGE LABEL

PRINCIPAL DISPLAY PANEL – 45 g Carton

NDC 68682-271-45

Rx only

HYDROCORTISONE BUTYRATE OINTMENT
0.1%

For topical use only.
Not for ophthalmic use.

Net Wt. 45 g

OCEANSIDE
PHARMACEUTICALS